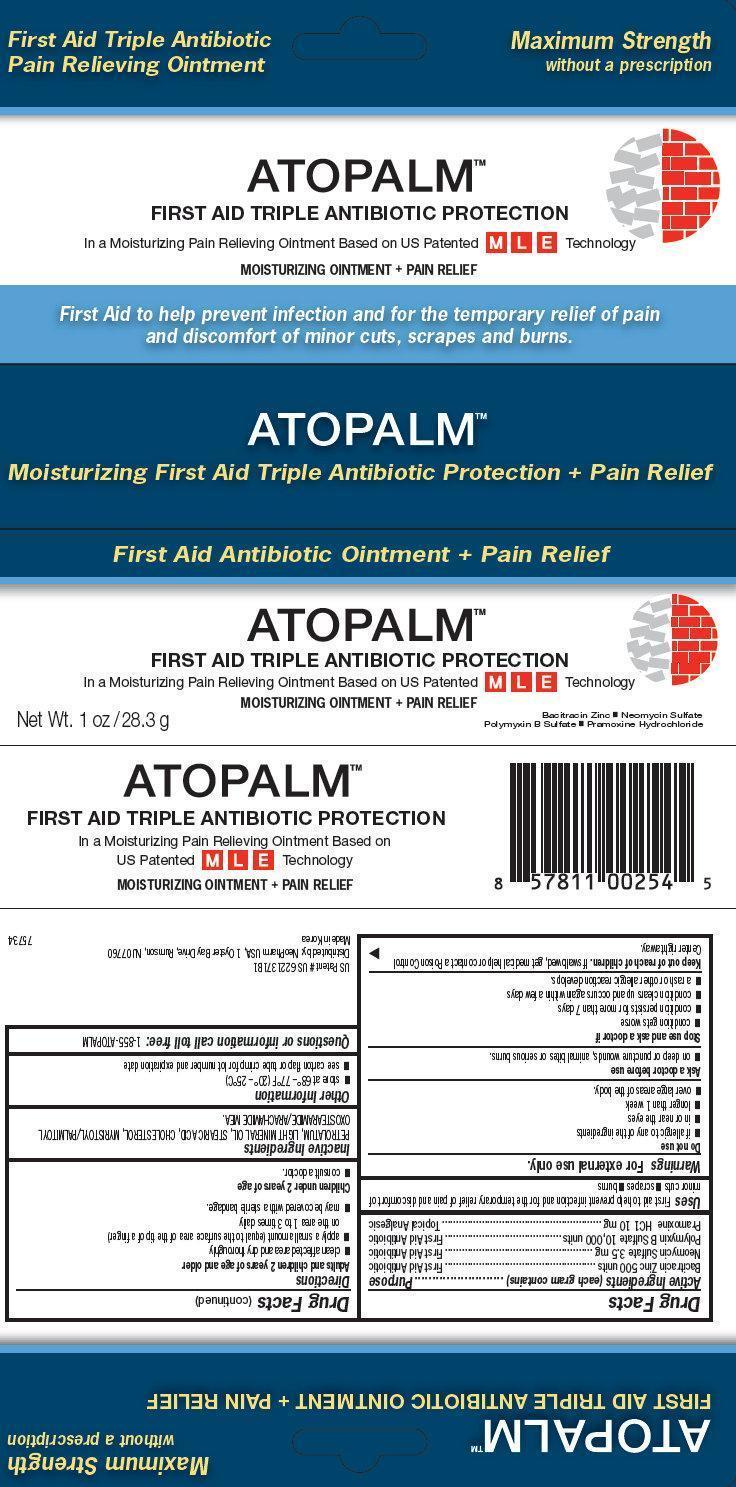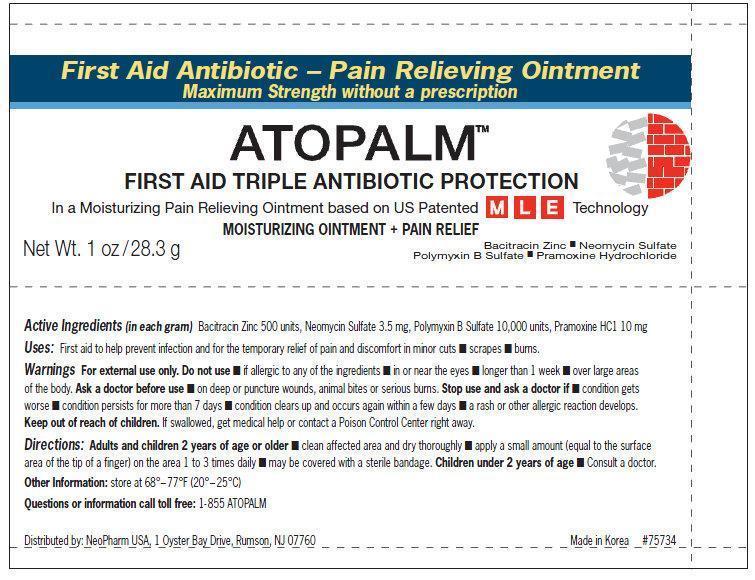 DRUG LABEL: ATOPALM FIRST AID TRIPLE ANTIBIOTIC PROTECTION MOISTURIZING AND PAIN RELIEF 
                
NDC: 51141-0238 | Form: OINTMENT
Manufacturer: Neopharm Co., Ltd.
Category: otc | Type: HUMAN OTC DRUG LABEL
Date: 20150617

ACTIVE INGREDIENTS: BACITRACIN ZINC 500 [iU]/1 g; NEOMYCIN SULFATE 3.5 mg/1 g; POLYMYXIN B SULFATE 10000 [iU]/1 g; PRAMOXINE HYDROCHLORIDE 10 mg/1 g
INACTIVE INGREDIENTS: PETROLATUM; LIGHT MINERAL OIL; CHOLESTEROL; STEARIC ACID; MYRISTOYL/PALMITOYL OXOSTEARAMIDE/ARACHAMIDE MEA

ATOPALM FIRST AID TRIPLE ANTIBIOTIC PROTECTION MOISTURIZING OINTMENT AND PAIN RELIEF

Active Ingredients (each gram contains)

Bacitracin Zinc 500 units

Neomycin Sulfate 3.5mg

Polymycin B Sulfate 10,000 units

Pramoxine HCl 10mg

Purpose

First Aid Antibiotic
Topical Analgesic

Uses

First aid to help prevent infection and for the temporary relief of pain and discomfort of minor cuts, scrapes, burns.

Warnings

For external use only

Do not use

- if you are allergic to any of the ingredients
- in or near the eyes
- longer than 1 week
- over large areas of the body

Ask a doctor before use

- on deep or puncture wounds, animal bites or serious burns

Stop use and ask a doctor if

- condition gets worse
- condition persists for more than 7 days
- condition clears up and occurs again within a few days
- a rash or other allergic reaction develops.

Keep out of reach of children.

If swallowed, get medical help or contact a Poison Control Center right away.

Directions

Adults and children 2 years of age and older

- clean the affected area and dry throughly
- apply a small amount (equal to the surface area of the tip of a finger) on the area 1 to 3 times daily
- may be covered with a sterile bandage

Children under 2 yrs. of age

- Consult a doctor.

Other Information

- store at 68° – 77°F (20° – 25°C)
- see carton flap or tube crimp for lot number and expiration date

Inactive Ingredients

PETROLATUM, LIGHT MINERAL OIL, STEARIC ACID, CHOLESTEROL, MYRISTOYL/PALMITOYL OXOSTEARAMIDE/ARACHMIDE MEA.

Questions or information call toll free:

Call 1-855-ATOPALM